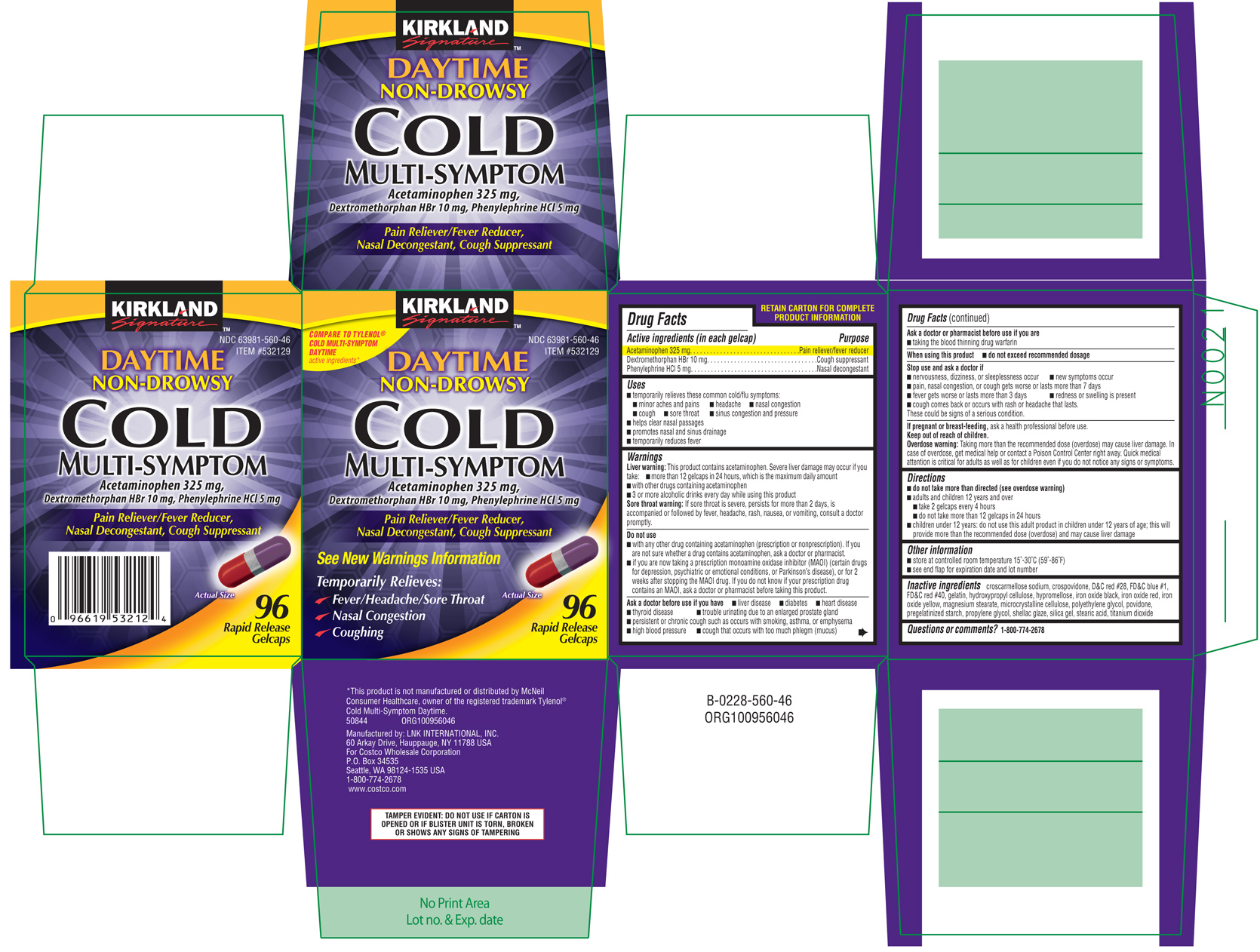 DRUG LABEL: Multi-Symptom Daytime Cold 
NDC: 63981-560 | Form: CAPSULE, LIQUID FILLED
Manufacturer: COSTCO WHOLESALE CORPORATION
Category: otc | Type: HUMAN OTC DRUG LABEL
Date: 20100924

ACTIVE INGREDIENTS: Acetaminophen 325 mg/1 1; Dextromethorphan Hydrobromide 10 mg/1 1; Phenylephrine Hydrochloride 5 mg/1 1
INACTIVE INGREDIENTS: Croscarmellose Sodium; Crospovidone; D&c Red No. 28; Fd&c Blue No. 1; Fd&c Red No. 40; Gelatin; Hydroxypropyl Cellulose; HYPROMELLOSES; Ferrosoferric Oxide; Ferric Oxide Yellow; Magnesium Stearate; Cellulose, Microcrystalline; Polyethylene Glycol; Povidone; Propylene Glycol; Silicon Dioxide; Stearic Acid; Titanium Dioxide

Active ingredients

(in each gelcap)

Acetaminophen 325 mg

Dextromethorphan HBr 10 mg

Phenylephrine HCl 5 mg

Purpose

Pain reliever/fever reducer

Cough suppressant

Nasal decongestant

Uses

- temporarily relieves these common cold/flu symptoms:
- minor aches and pains
- headache
- nasal congestion
- cough
- sore throat
- sinus congestion and pressure
- helps clear nasal passages
- promotes nasal and sinus drainage
- temporarily reduces fever

Warnings

Liver warning: This product contains acetaminophen. Severe liver damage may occur if you take:

- more than 12 gelcaps in 24 hours, which is the maximum daily amount
- with other drugs containing acetaminophen
- 3 or more alcoholic drinks every day while using this product

Sore throat warning: If sore throat is severe, persists for more than 2 days, is accompanied or followed by fever, headache, rash, nausea, or vomiting, consult a doctor promptly.

Do not use

- with any other drug containing acetaminophen (prescription or nonprescription). If you are not sure whether a drug contains acetaminophen, ask a doctor or pharmacist.
- if you are now taking a presciption monoamine oxidase inhibitor (MAOI) (certain drugs for depression, psychiatric or emotional conditions, or Parkinson's disease), or for 2 weeks after stopping the MAOI drug. If you do not know if your prescription drug contains an MAOI, ask a doctor or pharmacist before taking this product.

Ask a doctor before use if you have

- liver disease
- diabetes
- heart disease
- thyroid disease
- trouble urinating due to an enlarged prostate gland
- persistent or chronic cough such as occurs with smoking, asthma, or emphysema
- high blood pressure
- cough that occurs with too much phlegm (mucus)

Ask a doctor or pharmacist before use if you are

- taking the blood thinning drug warfarin

When using this product

- do not exceed recommended dosage

Stop use and ask a doctor if

- nervousness, dizziness, or sleeplessness occur
- new symptoms occur
- pain, nasal congestion, or cough gets worse or lasts more than 7 days
- fever gets worse or lasts more than 3 days
- redness or swelling is present
- cough comes back or occurs with rash or headache that lasts

These could be signs of a serious condition.

If pregnant or breast-feeding,

ask a health professional before use.

Keep out of reach of children.

Overdose warning: Taking more than the recommended dose (overdose) may cause liver damage. In case of overdose, get medical help or contact a Poison Control Center right away. Quick medical attention is critical for adults as well as for children even if you do not notice any signs or symptoms.

Directions

- do not take more than directed (see overdose warning)
- adults and children 12 years and over
- take 2 gelcaps every 4 hours
- do not take more than 12 gelcaps in 24 hours
- children under 12 years: do not use this adult product in children under 12 years of age; this will provide more than the recommended dose (overdose) and may cause liver damage

Other information

- store at controlled room temperature 15°-30°C (59°-86°F)
- see end flap for expiration date and lot number

Inactive ingredients

croscarmellose sodium, crospovidone, D&C red #28, FD&C blue #1, FD&C red #40, gelatin, hydroxypropyl cellulose, hypromellose, iron oxide black, iron oxide red, iron oxide yellow, magnesium stearate, microcrystalline cellulose, polyethylene glycol, povidone, pregelatinized starch, propylene glycol, shellac glaze, silica gel, stearic acid, titanium dioxide

Questions or comments?

1-800-774-2678

PRODUCT PACKAGING

The product packaging shown below represents a sample of that currently in use. Additional packaging may also be available.

KIRKLAND

Signature™

COMPARE TO TYLENOL®

COLD MULTI-SYMPTOMS DAYTIME

active ingredients*

NDC 63981-560-46

ITEM #532129

DAYTIME

NON-DROWSY

COLD

MULTI-SYMPTOM

Acetaminophen 325 mg,

Dextromethorphan HBr 10 mg, Phenylephrine HCl 5 mg

Pain Reliever/Fever Reducer,

Nasal Decongestant, Cough Suppressant

See New Warnings Information

Temporarily Relieves:

√ Fever / Headache / Sore Throat

√ Nasal Congestion

√ Coughing

Actual Size

96

Rapid Release

Gelcaps

TAMPER EVIDENT: DO NOT USE IF CARTON IS OPENED OR IF BLISTER UNIT IS TORN, BROKEN OR SHOWS ANY SIGNS OF TAMPERING

50844 ORG100956046

Manufactured by: LNK INTERNATIONAL, INC.

60 Arkay Drive, Hauppauge, NY 11788 USA

For Costco Wholesale Corporation

P.O. Box 34535

Seattle, WA 98124-1535 USA

1-800-774-2678

www.costco.com